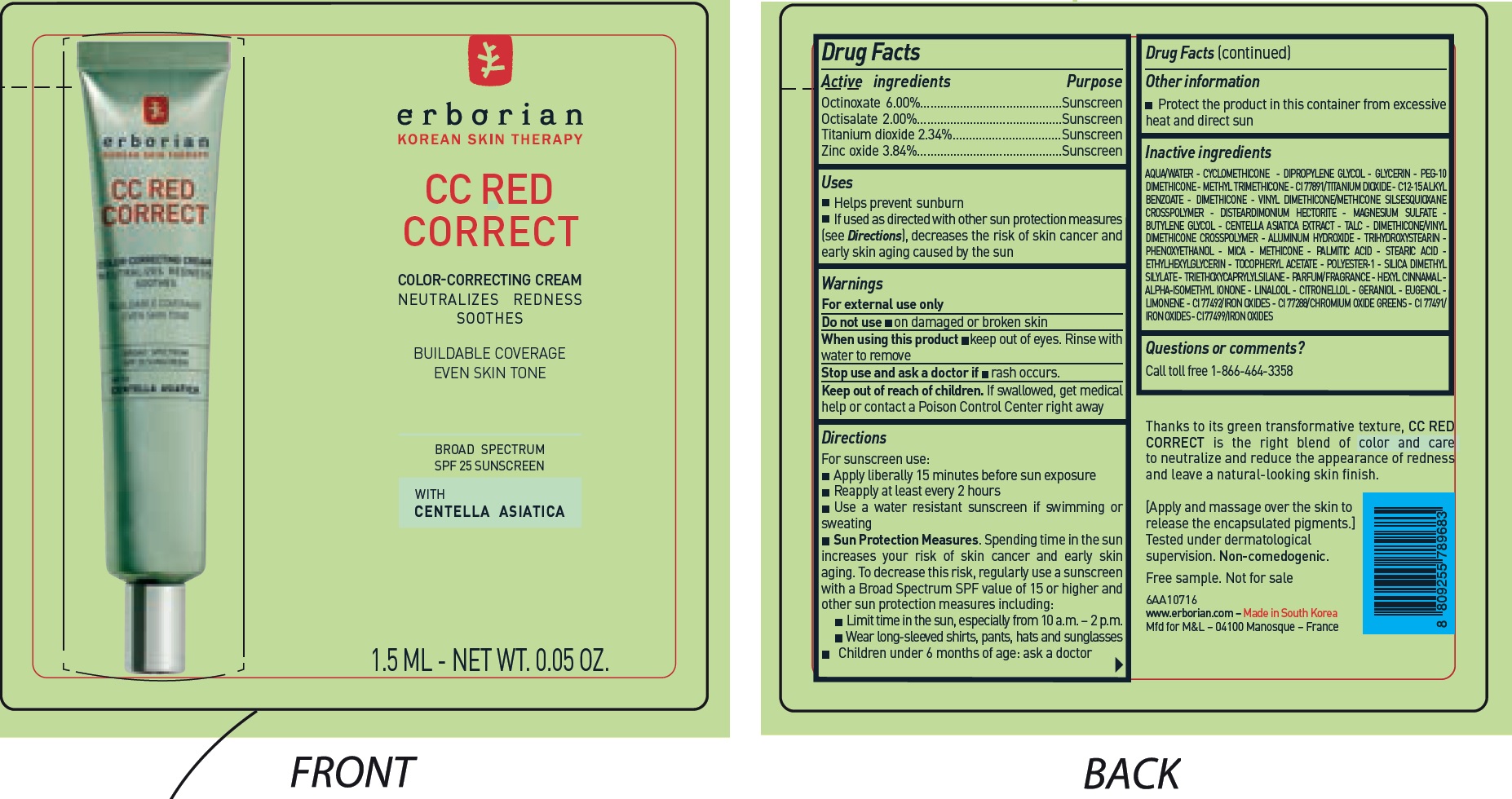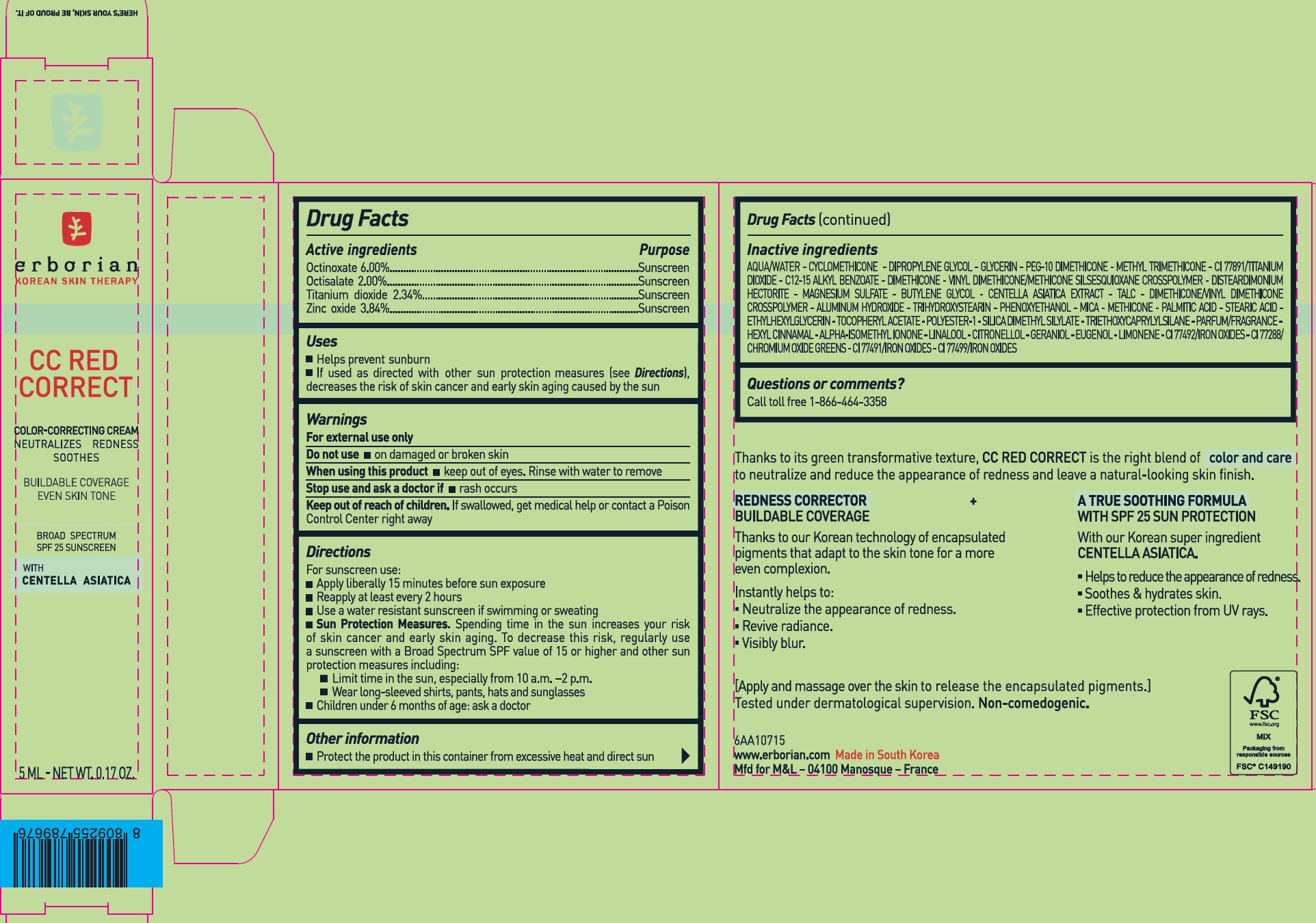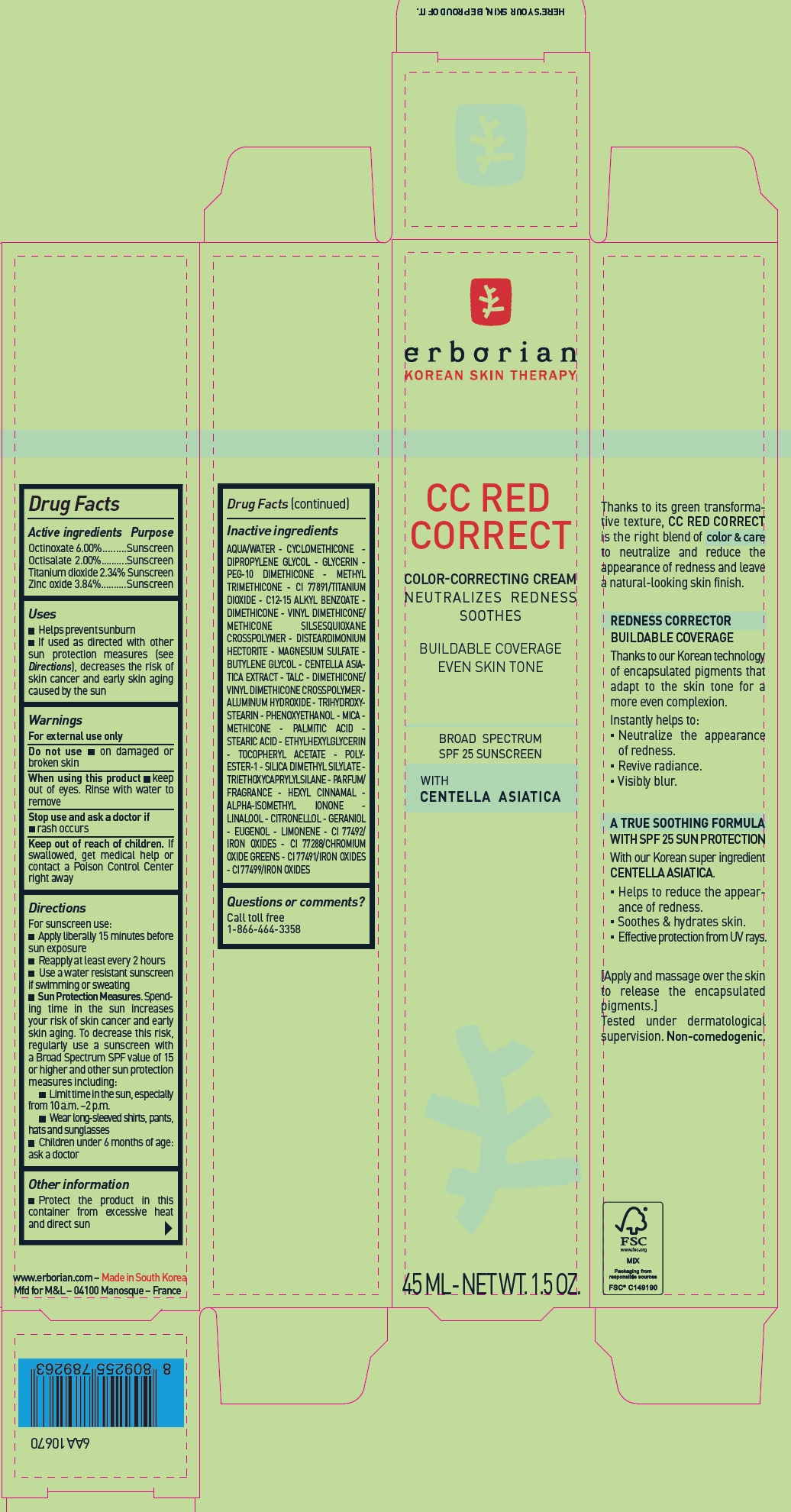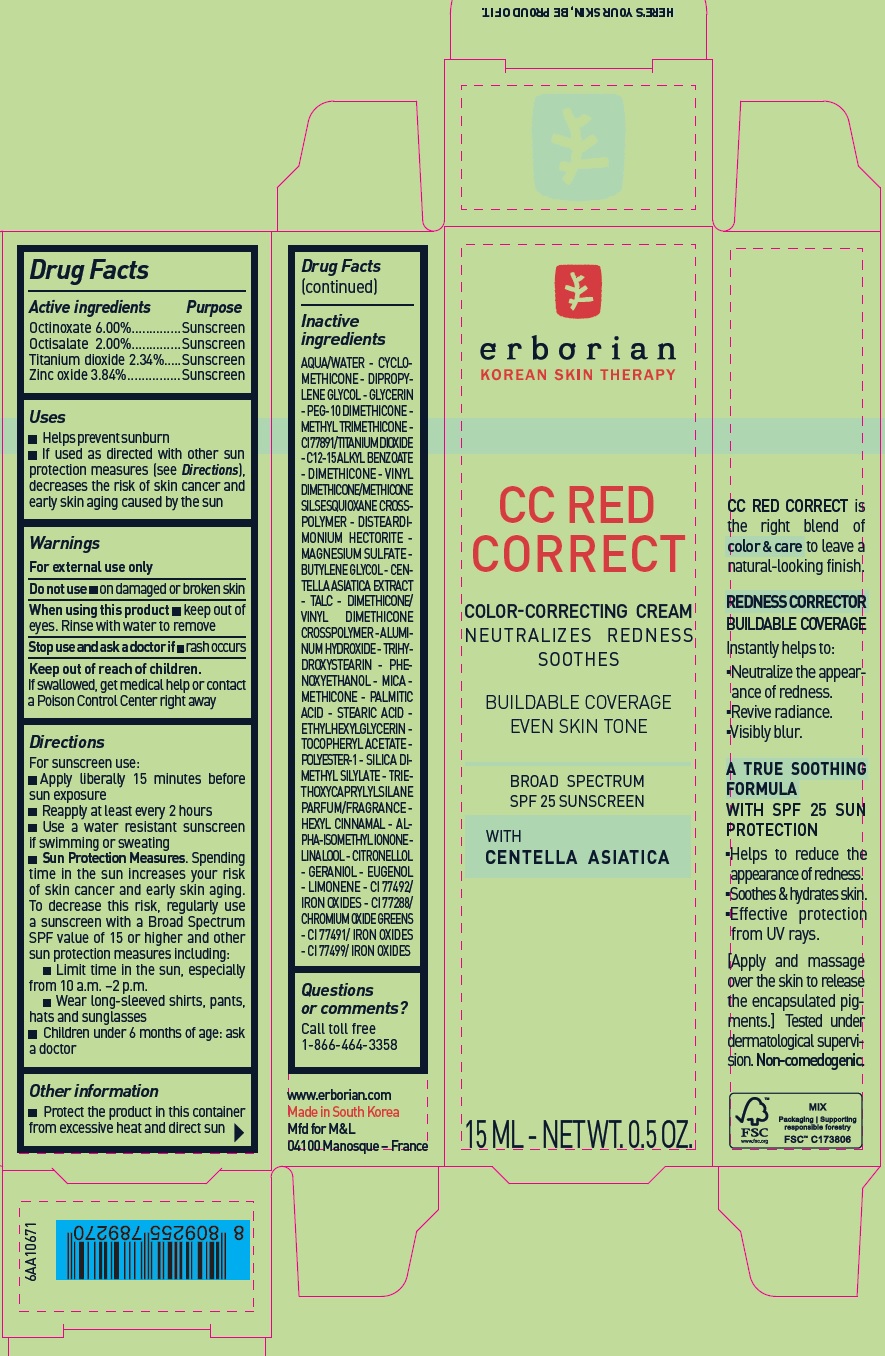 DRUG LABEL: ERBORIAN CC Red Correct Color Correcting SPF 25
NDC: 10345-953 | Form: CREAM
Manufacturer: LABORATOIRES M&L
Category: otc | Type: HUMAN OTC DRUG LABEL
Date: 20250812

ACTIVE INGREDIENTS: OCTINOXATE 60 mg/1 mL; OCTISALATE 20 mg/1 mL; TITANIUM DIOXIDE 23.4 mg/1 mL; ZINC OXIDE 38.4 mg/1 mL
INACTIVE INGREDIENTS: WATER; CYCLOMETHICONE; DIPROPYLENE GLYCOL; GLYCERIN; METHYL TRIMETHICONE; C12-15 ALKYL BENZOATE; DIMETHICONE; VINYL DIMETHICONE/METHICONE SILSESQUIOXANE CROSSPOLYMER; DISTEARDIMONIUM HECTORITE; MAGNESIUM SULFATE; BUTYLENE GLYCOL; CENTELLA ASIATICA TRITERPENOIDS; TALC; ALUMINUM HYDROXIDE; TRIHYDROXYSTEARIN; PHENOXYETHANOL; MICA; PALMITIC ACID; STEARIC ACID; ETHYLHEXYLGLYCERIN; .ALPHA.-TOCOPHEROL ACETATE; SILICA DIMETHYL SILYLATE; TRIETHOXYCAPRYLYLSILANE; .ALPHA.-HEXYLCINNAMALDEHYDE; ISOMETHYL-.ALPHA.-IONONE; LINALOOL, (+/-)-; CITRONELLOL; GERANIOL; EUGENOL; LIMONENE, (+)-; FERRIC OXIDE YELLOW; CHROMIC OXIDE; FERRIC OXIDE RED; FERROSOFERRIC OXIDE

ERBORIAN CC Red Correct Color Correcting Cream SPF 25

Active ingredients

Octinoxate 6.00%
Octisalate 2.00%
Titanium dioxide 2.34%
Zinc oxide 3.84%

Purpose

Sunscreen

Uses

- Helps prevent sunburn
- If used as directed with other sun protection measures (see Directions), decreases the risk of skin cancer and early skin aging caused by the sun

Warnings

For external use only

Do not use

- on damaged or broken skin

When using this product

- keep out of eyes. Rinse with water to remove

Stop use and ask a doctor if

- rash occurs

Keep out of reach of children.

If swallowed, get medical help or contact a Poison Control Center right away

Directions

For sunscreen use:

- Apply liberally 15 minutes before sun exposure
- Reapply at least every 2 hours
- Use a water resistant sunscreen if swimming or sweating
- Sun Protection Measures.Spending time in the sun increases your risk of skin cancer and early skin aging. To decrease this risk, regularly use a sunscreen with a Broad Spectrum SPF value of 15 or higher and other sun protection measures including:
- Limit time in the sun, especially from 10 a.m. –2 p.m.
- Wear long-sleeved shirts, pants, hats and sunglasses
- Children under 6 months of age: ask a doctor

Other information

- Protect the product in this container from excessive heat and direct sun

Inactive ingredients

AQUA/WATER - CYCLOMETHICONE - DIPROPYLENE GLYCOL - GLYCERIN - PEG-10 DIMETHICONE - METHYL TRIMETHICONE - CI 77891/TITANIUM DIOXIDE - C12-15 ALKYL BENZOATE - DIMETHICONE - VINYL DIMETHICONE/METHICONE SILSESQUIOXANE CROSSPOLYMER - DISTEARDIMONIUM HECTORITE - MAGNESIUM SULFATE - BUTYLENE GLYCOL - CENTELLA ASIATICA EXTRACT - TALC - DIMETHICONE/VINYL DIMETHICONE CROSSPOLYMER - ALUMINUM HYDROXIDE - TRIHYDROXYSTEARIN - PHENOXYETHANOL - MICA - METHICONE - PALMITIC ACID - STEARIC ACID - ETHYLHEXYLGLYCERIN - TOCOPHERYL ACETATE - POLYESTER-1 - SILICA DIMETHYL SILYLATE - TRIETHOXYCAPRYLYLSILANE - PARFUM/FRAGRANCE - HEXYL CINNAMAL - ALPHA-ISOMETHYL IONONE - LINALOOL - CITRONELLOL - GERANIOL - EUGENOL - LIMONENE - CI 77492/IRON OXIDES - CI 77288/CHROMIUM OXIDE GREENS - CI 77491/ IRON OXIDES - CI 77499/IRON OXIDES

Questions or comments?

Call toll free 1-866-464-3358